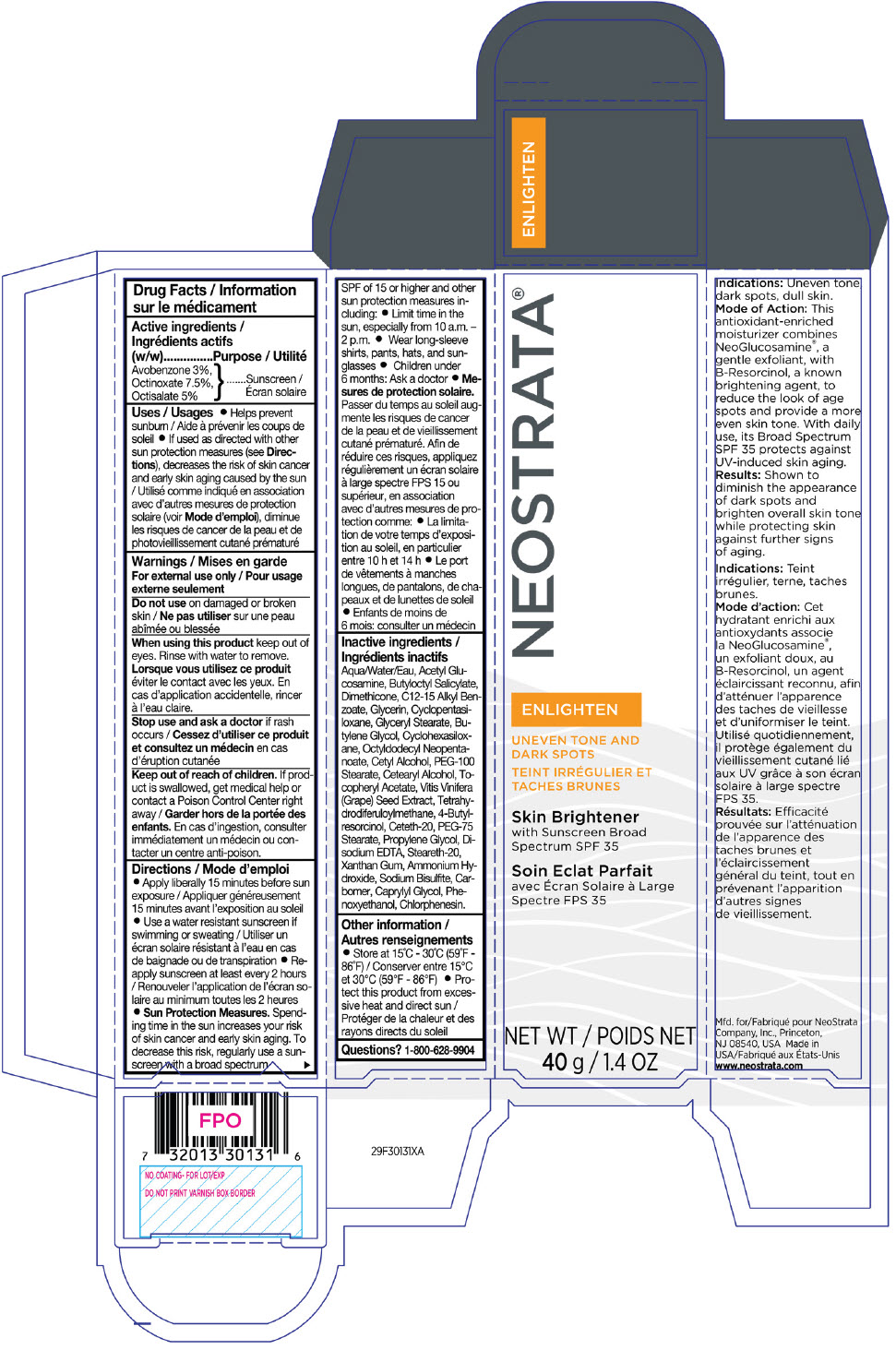 DRUG LABEL: NeoStrata Enlighten Skin Brightener
NDC: 58414-0019 | Form: CREAM
Manufacturer: NeoStrata Company Inc.
Category: otc | Type: HUMAN OTC DRUG LABEL
Date: 20250110

ACTIVE INGREDIENTS: OCTINOXATE 75 mg/1 g; OCTISALATE 50 mg/1 g; AVOBENZONE 30 mg/1 g
INACTIVE INGREDIENTS: WATER; N-ACETYLGLUCOSAMINE; BUTYLOCTYL SALICYLATE; DIMETHICONE; ALKYL (C12-15) BENZOATE; GLYCERIN; CYCLOMETHICONE 5; GLYCERYL MONOSTEARATE; BUTYLENE GLYCOL; CYCLOMETHICONE 6; OCTYLDODECYL NEOPENTANOATE; CETYL ALCOHOL; PEG-100 STEARATE; CETOSTEARYL ALCOHOL; VITIS VINIFERA SEED; .ALPHA.-TOCOPHEROL ACETATE; PROPYLENE GLYCOL; EDETATE DISODIUM ANHYDROUS; 4-BUTYLRESORCINOL; TETRAHYDRODIFERULOYLMETHANE; PEG-75 STEARATE; STEARETH-20; CETETH-20; XANTHAN GUM; SODIUM BISULFITE; AMMONIA; CAPRYLYL GLYCOL; PHENOXYETHANOL; CHLORPHENESIN

NeoStrata®Enlighten Skin Brightener
with Sunscreen Broad Spectrum SPF 35

Drug Facts

Active ingredients (w/w)

Avobenzone 3%, Octinoxate 7.5%, Octisalate 5%

Purpose

Sunscreen

Uses

- Helps prevent sunburn
- If used as directed with other sun protection measures (see Directions), decreases the risk of skin cancer and early skin aging caused by the sun

Warnings

For external use only

Do not use on damaged or broken skin

WHEN USING

When using this productkeep out of eyes. Rinse with water to remove.

Stop use and ask a doctorif rash occurs

Keep out of reach of children.If product is swallowed, get medical help or contact a Poison Control Center right away.

Directions

- Apply liberally 15 minutes before sun exposure
- Use a water resistant sunscreen if swimming or sweating
- Reapply sunscreen at least every 2 hours
- Sun Protection Measures.Spending time in the sun increases your risk of skin cancer and early skin aging. To decrease this risk, regularly use a sunscreen with a broad spectrum SPF of 15 or higher and other sun protection measures including:
  - Limit time in the sun, especially from 10 a.m.–2 p.m.
  - Wear long-sleeve shirts, pants, hats, and sunglasses
- Children under 6 months: Ask a doctor

Inactive ingredients

Water, Acetyl Glucosamine, Butyloctyl Salicylate, Dimethicone, C12-15 Alkyl Benzoate, Glycerin, Cyclopentasiloxane, Glyceryl Stearate, Butylene Glycol, Cyclohexasiloxane, Octyldodecyl Neopentanoate, Cetyl Alcohol, PEG-100 Stearate, Cetearyl Alcohol, Tocopheryl Acetate, Vitis Vinifera (Grape) Seed Extract, Tetrahydrodiferuloylmethane, 4-Butyl-resorcinol, Ceteth-20, PEG-75 Stearate, Propylene Glycol, Disodium EDTA, Steareth-20, Xanthan Gum, Ammonium Hydroxide, Sodium Bisulfite, Carbomer, Caprylyl Glycol, Phenoxyethanol, Chlorphenesin.

Other information

- Store at 15°C-30°C (59°F-86°F)
- Protect this product from excessive heat and direct sun

Questions?

1-800-628-9904

PRINCIPAL DISPLAY PANEL - 40 g Tube Carton

NEOSTRATA®
ENLIGHTEN
UNEVEN TONE AND
DARK SPOTS
Skin Brightener
with Sunscreen Broad
Spectrum SPF 35
NET WT
40 g / 1.4 OZ